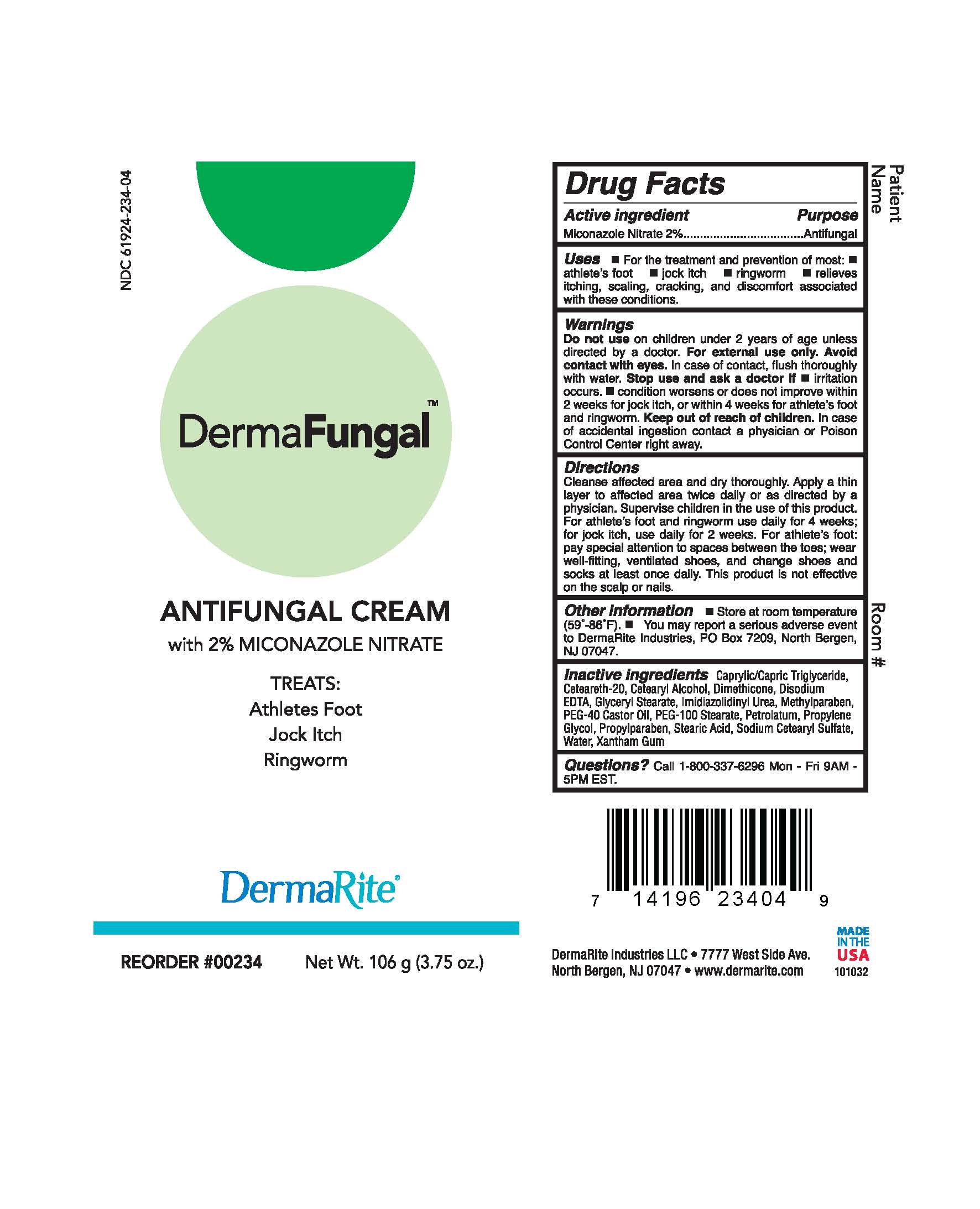 DRUG LABEL: DERMAFUNGAL
NDC: 61924-234 | Form: CREAM
Manufacturer: DermaRite industries, LLC
Category: otc | Type: HUMAN OTC DRUG LABEL
Date: 20241205

ACTIVE INGREDIENTS: MICONAZOLE NITRATE 0.02 g/100 g
INACTIVE INGREDIENTS: MEDIUM-CHAIN TRIGLYCERIDES; POLYOXYL 20 CETOSTEARYL ETHER; CETOSTEARYL ALCOHOL; IMIDUREA; DIMETHICONE; EDETATE DISODIUM; GLYCERYL MONOSTEARATE; METHYLPARABEN; PEG-40 CASTOR OIL; PEG-100 STEARATE; PETROLATUM; PROPYLENE GLYCOL; PROPYLPARABEN; STEARIC ACID; WATER; XANTHAN GUM

DRUG LISTING: DERMAFUNGAL

Active Ingredient:

Miconazole Nitrate 2%

Purpose:

Antifungal

Uses:

- For the treatment and prevention of most: athlete's foot, jock itch, ringworm
- relieves itching, scaling,cracking, and discomfort associated with these conditions.

Warnings:

- For external use only.
- Avoid contact with eyes. In case of contact, flush thoroughly with water.
- Stop use and ask doctor if irritation occurs , condition worsens or does not improve in 2 weeks for jock itch, or within 4 weeks for athlete's foot and ringworm.

Warnings

- Keep out of reach of children. In case of accidental ingestion contact physician or Poison Control Center right away.

Directions

Cleanse affected area and dry thoroughly. Apply a thin layer to affected area twice daily or as directed by physician.

- For jockitch use daily for two weeks.
- For athelete's foot use daily for four weeks.

Other Information:

- This product is not effective on the scalp and nails.
- Store at room temperature (59°-86°F)

Inactive Ingredients:

Caprylic/Capric Triglyceride, Ceteareth-20, Disodium EDTA, Glyceryl Stearate, Methylparaben, PEG-40 Castor Oil, PEG-100 Stearate, Petrolatum, Propylene Glycol, Propylparaben, Stearic Acid, Water, Xantham Gum